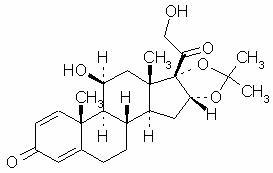 DRUG LABEL: Unknown
Manufacturer: SkinMedica
Category: prescription | Type: HUMAN PRESCRIPTION DRUG LABELING
Date: 20070330

Desonate™ (desonide) Gel 0.05%
Rx Only
FOR TOPICAL USE ONLY.
NOT FOR OPHTHALMIC, ORAL, OR INTRAVAGINAL USE.

DESCRIPTION

Desonate Gel contains desonide (pregna-1,4-diene-3, 20-dione,11, 21-dihydroxy-16, 17-[(1-methylethylidene) bis(oxy)]-, (11ß,16α)- a synthetic nonfluorinated corticosteroid for topical dermatologic use. Chemically, desonide is C24H32O6. It has the following structural formula:

Desonide has the molecular weight of 416.52. It is a white to off-white odorless powder which is soluble in methanol and practically insoluble in water.

Each gram of Desonate Gel contains 0.5 mg of desonide in an aqueous gel base of purified water, glycerin, propylene glycol, edetate disodium dihydrate, methylparaben, propylparaben, sodium hydroxide, and Carbopol® 981.

CLINICAL PHARMACOLOGY

Topical corticosteroids share anti-inflammatory, antipruritic and vasoconstrictive properties. The mechanism of the anti-inflammatory activity of the topical steroids, in general, is unclear. However, corticosteroids are thought to act by the induction of phospholipase A2 inhibitory proteins, collectively called lipocortins. It is postulated that these proteins control the biosynthesis of potent mediators of inflammation such as prostaglandins and leukotrienes by inhibiting the release of their common precursor arachidonic acid. Arachidonic acid is released from membrane phospholipids by phospholipase A2.

Pharmacokinetics

The extent of percutaneous absorption of topical corticosteroids is determined by many factors, including product formulation and the integrity of the epidermal barrier. Occlusion, inflammation and/or other disease processes in the skin may also increase percutaneous absorption. Topical corticosteroids can be absorbed from normal intact skin. Once absorbed through the skin, topical corticosteroids are handled through pharmacokinetic pathways similar to systemically administered corticosteroids. They are metabolized primarily in the liver and then are excreted by the kidneys. Some corticosteroids and their metabolites are also excreted in the bile.

In a controlled pharmacokinetic study, one of 37 (3%) pediatric subjects with moderate to severe atopic dermatitis covering at least 35% body surface area who applied Desonate Gel experienced suppression of the adrenal glands following 4 weeks of therapy (seePRECAUTIONS: General andPediatric Use). A follow-up evaluation of the subject’s adrenal axis was not performed; it is unknown whether the suppression was reversible.

CLINICAL STUDIES

In two randomized vehicle-controlled clinical studies, patients 3 months to 18 years of age with mild to moderate atopic dermatitis were treated twice daily for 4 weeks with either Desonate Gel or vehicle. Treatment success was defined as achieving clear or almost clear on the Investigator’s Global Severity Score (IGSS) with at least a 2 point change (decrease) from the subject’s baseline IGSS when compared to the Week 4 IGSS. The results of the 2 clinical trials are summarized in Table 1:

Table 1. Subjects Achieving Treatment Success
Clinical Trial 1 |  | Clinical Trial 2
Desonate Gel | Vehicle | Desonate Gel | Vehicle
N = 289 | N = 92 | N = 136 | N = 65
128 (44%) | 13 (14%) | 38 (28%) | 4 (6%)

INDICATIONS AND USAGE

Desonate Gel is indicated for the treatment of mild to moderate atopic dermatitis in patients 3 months of age and older. Patients should be instructed to use Desonate Gel for the minimum amount of time as necessary to achieve the desired results because of the potential for Desonate Gel to suppress the hypothalamic-pituitary-adrenal (HPA) axis (seePRECAUTIONS). Treatment should not exceed 4 consecutive weeks.

CONTRAINDICATIONS

Desonate Gel is contraindicated in those patients with a history of hypersensitivity to any of the components of the preparation.

PRECAUTIONS

General

The safety of Desonate Gel has not been established beyond 4 weeks of use.

Systemic absorption of topical corticosteroids can produce reversible hypothalamic-pituitary-adrenal (HPA) axis suppression with the potential for glucocorticosteroid insufficiency after withdrawal of treatment. Manifestations of Cushing's syndrome, hyperglycemia, and glucosuria can also be produced in some patients by systemic absorption of topical corticosteroids while on treatment.

Conditions which augment systemic absorption include the application of topical corticosteroids, over large body surface areas, prolonged use, or the addition of occlusive dressings. Therefore, patients applying a topical corticosteroid to a large body surface area or to areas under occlusion should be evaluated periodically for evidence of HPA axis suppression (seeLaboratory Tests).

If HPA axis suppression is noted, an attempt should be made to withdraw the drug, to reduce the frequency of application, or to substitute a less potent corticosteroid. Recovery of HPA axis function is generally prompt and complete upon discontinuation of topical corticosteroids. Infrequently, signs and symptoms of glucocorticosteroid insufficiency may occur, requiring supplemental systemic corticosteroids. For information on systemic supplementation, see prescribing information for those products.

The effect of Desonate Gel on HPA axis function was investigated in pediatric subjects, 6 months to 6 years old, with atopic dermatitis covering at least 35% of their body, who were treated with Desonate Gel twice daily for 4 weeks. One of 37 subjects (3%) displayed adrenal suppression after 4 weeks of use, based on the cosyntropin stimulation test. As follow-up evaluation of the subject’s adrenal axis was not performed, it is unknown whether the suppression was reversible.

Pediatric patients may be more susceptible to systemic toxicity from equivalent doses due to their larger skin surface to body mass ratios (seePRECAUTIONS - Pediatric use).

If irritation develops, Desonate Gel should be discontinued and appropriate therapy instituted. Allergic contact dermatitis with corticosteroids is usually diagnosed by observing failure to heal rather than noting a clinical exacerbation as with most topical products not containing corticosteroids. Such an observation should be corroborated with appropriate diagnostic patch testing.

If concomitant skin infections are present or develop, an appropriate antifungal or antibacterial agent should be used. If a favorable response does not occur promptly, use of Desonate Gel should be discontinued until the infection has been adequately controlled.

Information for Patients

Patients using topical corticosteroids should receive the following information and instructions:

- This medication is to be used as directed by the physician. It is for external use only. Avoid contact with the eyes.
- This medication should not be used for any disorder other than that for which it was prescribed.
- Unless directed by the physician, the treated skin area should not be bandaged or otherwise covered or wrapped so as to be occlusive.
- Unless directed by a physician, this medication should not be used on the underarm or groin areas of pediatric patients.
- Parents of pediatric patients should be advised not to use Desonate Gel in the treatment of diaper dermatitis. Desonate Gel should not be applied in the diaper area, as diapers or plastic pants may constitute occlusive dressing (seeDOSAGE AND ADMINISTRATION).
- Patients should report to their physician any signs of local adverse reactions.
- Other corticosteroid-containing products should not be used with Desonate Gel without first consulting with the physician.
- As with other corticosteroids, therapy should be discontinued when control is achieved. If no improvement is seen within 4 weeks, contact the physician.

Laboratory Tests

The cosyntropin (ACTH1-24) stimulation test may be helpful in evaluating patients for HPA axis suppression.

Carcinogenesis, Mutagenesis, and Impairment of Fertility

Long-term animal studies have not been performed to evaluate the carcinogenic or photoco-carcinogenic potential of Desonate Gel or the effect on fertility of desonide.

Desonide revealed no evidence of mutagenic potential based on the results of an in vitro genotoxicity test (Ames assay) and an in vivo genotoxicity test (mouse micronucleus assay). Desonide was positive without S9 activation and was equivocal with S9 activation in an in vitro mammalian cell mutagenesis assay (L5178Y/TK^+ mouse lymphoma assay). A dose response trend was not noted in this assay.

Pregnancy

Teratogenic Effects

Pregnancy Category C:

Corticosteroids have been shown to be teratogenic in laboratory animals when administered systemically at relatively low-dosage levels. Some corticosteroids have been shown to be teratogenic after dermal application in laboratory animals.

There are no adequate and well-controlled studies in pregnant women. Therefore, Desonate Gel should be used during pregnancy only if the potential benefit justifies the potential risk to the fetus.

No reproductive studies in animals have been performed with Desonate Gel. Dermal embryofetal development studies were conducted in rats and rabbits with a desonide cream, 0.05% formulation. Topical doses of 0.2, 0.6, and 2.0 g cream/kg/day of a desonide cream, 0.05% formulation or 2.0 g/kg of the cream base were administered topically to pregnant rats (gestational days 6-15) and pregnant rabbits (gestational days 6 18). Maternal body weight loss was noted at all dose levels of the desonide cream, 0.05% formulation in rats and rabbits. Teratogenic effects characteristic of corticosteroids were noted in both species. The desonide cream, 0.05% formulation was teratogenic in rats at topical doses of 0.6 and 2.0 g cream/kg/day and in rabbits at a topical dose of 2.0 g cream/kg/day. No teratogenic effects were noted for the desonide cream, 0.05% formulation at a topical dose of 0.2 g cream/kg/day in rats and 0.6 g cream/kg/day in rabbits. These doses (0.2 g cream/kg/day and 0.6 g cream/kg/day) are similar to the maximum recommended human dose based on body surface area comparisons.

Nursing Mothers

Systemically administered corticosteroids appear in human milk and could suppress growth, interfere with endogenous corticosteroid production, or cause other untoward effects. It is not known whether topical administration of corticosteroids could result in sufficient systemic absorption to produce detectable quantities in human milk. Because many drugs are excreted in human milk, caution should be exercised when Desonate Gel is administered to a nursing woman.

Pediatric Use

Safety and effectiveness of Desonate Gel in pediatric patients less than 3 months of age have not been evaluated, and therefore its use in this age group is not recommended.

Because of a higher ratio of skin surface area to body mass, pediatric patients are at a greater risk than adults of HPA axis suppression when they are treated with topical corticosteroids. They are therefore also at greater risk of glucocorticosteroid insufficiency after withdrawal of treatment and of Cushing's syndrome while on treatment. Adverse effects, including striae, have been reported with inappropriate use of topical corticosteroids in infants and children. HPA axis suppression, Cushing's syndrome, linear growth retardation, delayed weight gain and intracranial hypertension have been reported in children receiving topical corticosteroids. Manifestations of adrenal suppression in children include low plasma cortisol levels and absence of response to ACTH stimulation. Manifestations of intracranial hypertension include bulging fontanelles, headaches, and bilateral papilledema.

The effect of Desonate Gel on HPA axis function was investigated in pediatric subjects, 6 months to 6 years old, with atopic dermatitis covering at least 35% of their body, who were treated with Desonate Gel twice daily for 4 weeks. One of 37 subjects (3%) displayed adrenal suppression after 4 weeks of use based on the cosyntropin stimulation test. As follow-up evaluation of the subject’s adrenal axis was not performed; it is unknown whether the suppression was reversible.

Geriatric Use

Clinical studies of Desonate Gel did not include patients aged 65 and older to determine if they respond differently than younger patients. Treatment of this patient population should reflect the greater frequency of decreased hepatic, renal, or cardiac function, and of concomitant disease or other drug therapy.

ADVERSE REACTIONS

In controlled clinical studies of 425 Desonate Gel treated subjects and 157 Vehicle-treated subjects, adverse events occurred at the application site in 3% of subjects treated with Desonate Gel and the incidence rate was not higher compared with vehicle-treated subjects. The most common local adverse events in Desonate Gel- treated subjects were application site burning in 1% (4/425) and rash in 1% (3/425) followed by application site pruritus in <1% (2/425) .

Adverse events that resulted in premature discontinuation of study drug in Desonate Gel treated subjects were telangiectasia and worsening of atopic dermatitis in one subject each. Additional adverse events observed during clinical trials for patients treated with Desonate Gel included headache in 2% (8/425) compared with 1% (2/157) in those treated with vehicle.

The following additional local adverse reactions have been reported infrequently with topical corticosteroids. They may occur more frequently with the use of occlusive dressings, especially with higher potency corticosteroids. These reactions are listed in an approximate decreasing order of occurrence: folliculitis, acneiform eruptions, hypopigmentation, perioral dermatitis, secondary infection, skin atrophy, striae, and miliaria.

OVERDOSAGE

Topically applied Desonate Gel can be absorbed in sufficient amounts to produce systemic effects (SeePRECAUTIONS).

DOSAGE AND ADMINISTRATION

Desonate Gel should be applied as a thin layer to the affected areas two times daily and rubbed in gently. Therapy should be discontinued when control is achieved. If no improvement is seen within 4 weeks, reassessment of diagnosis may be necessary. Treatment beyond 4 consecutive weeks is not recommended.

Desonate Gel should not be used with occlusive dressings.

HOW SUPPLIED

Desonate Gel is supplied in:
3.5g Sample-Not for Sale (NDC 67402-050-03)
60g (NDC 67402-050-60) tubes

STORAGE CONDITIONS: Store at controlled room temperature: 25°C (77°F), excursions permitted between 15° - 30°C (59°– 86°F).

Avoid contact with eyes or other mucous membranes
Keep out of reach of children

CAUTION: Federal law prohibits dispensing without a prescription.

________________________________________________________________________

Manufactured by:
CPL,
Buffalo, New York 14213
Distributed by:
SkinMedica
Carlsbad, CA 92010
866-867-0110; www.skinmedica.com

The Hydrogel Technology logo is a trademark of Dow Pharmaceutical Sciences, Inc.

Desonate is a trademark of SkinMedica.

03-6083 (flat)
03-6082 (folded)
10/2006